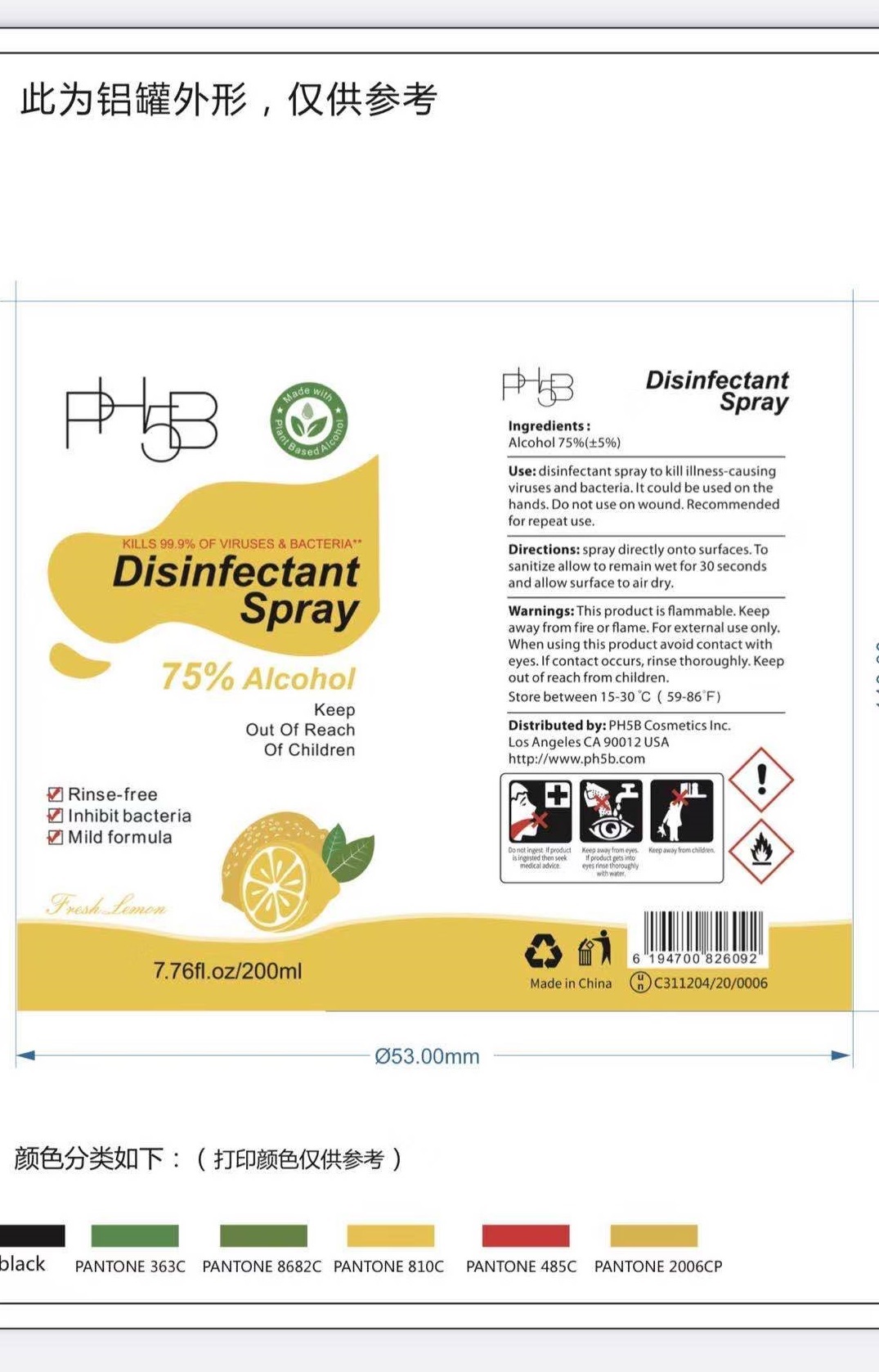 DRUG LABEL: DisinfectantSpray
NDC: 81276-201 | Form: SPRAY
Manufacturer: Dongyang Medical & Hygienic Articles Co., Ltd.
Category: otc | Type: HUMAN OTC DRUG LABEL
Date: 20210224

ACTIVE INGREDIENTS: ALCOHOL 150 mL/200 mL
INACTIVE INGREDIENTS: WATER; LEMON

81276-201 200ml DONGYANG MEDICAL

Active Ingredient(s)

Alcohol 75% v/v. Purpose: Antiseptic,difection

Inactive ingredients

Water, Lemon

Use

disinfectant spray to kill illness-causing viruses and bacteria. It could be used on the hands. Do not use on wound. Recommended for repeat use.

Warnings

This product is flammable. Keep away from fire or flam. For external use only. When using this product avoid contact with eyes. If contact occurs, rinse thoroughly. Keep out of reach from children.
Store between 15-30℃（59-86℉）

Do not use

On polished wood, leather, painted surfaces,rayon fabric, or acrylic plastics.

Purpose

Ensure surfaces are pre-clean before use.To disinfect,hold can upright for 6’’-8’’ from surface before spraying. Spray for 2-4 seconds until coverd with mist. Allow to airdry for 3-5 minutes.

When using this product keep out of eyes, ears, and mouth. In case of contact with eyes, rinse eyes thoroughly with water.
Stop use and ask a doctor if irritation or rash occurs. These may be signs of a serious condition.
Keep out of reach of children. If swallowed, get medical help or contact a Poison Control Center right away.

Stop use and ask a doctor if irritation or rash occurs. These may be signs of a serious condition.

Keep out of reach of children. If swallowed, get medical help or contact a Poison Control Center right away.

Directions

spray directly onto surfaces. To sanitize allow to remain wet for 30 seconds and allow surface to air dry.

Other information

- Store in original container in areas away from children. Keep securely closed.

ASK DOCTOR

If in eyes, hold eye open and rinse slowly and gently with water for 15-20 minutes.

Call a poiseon control center or doctor for treatment advice.

Package Label - Principal Display Panel

200 ml in 1 Bottle NDC: 81276-201-01